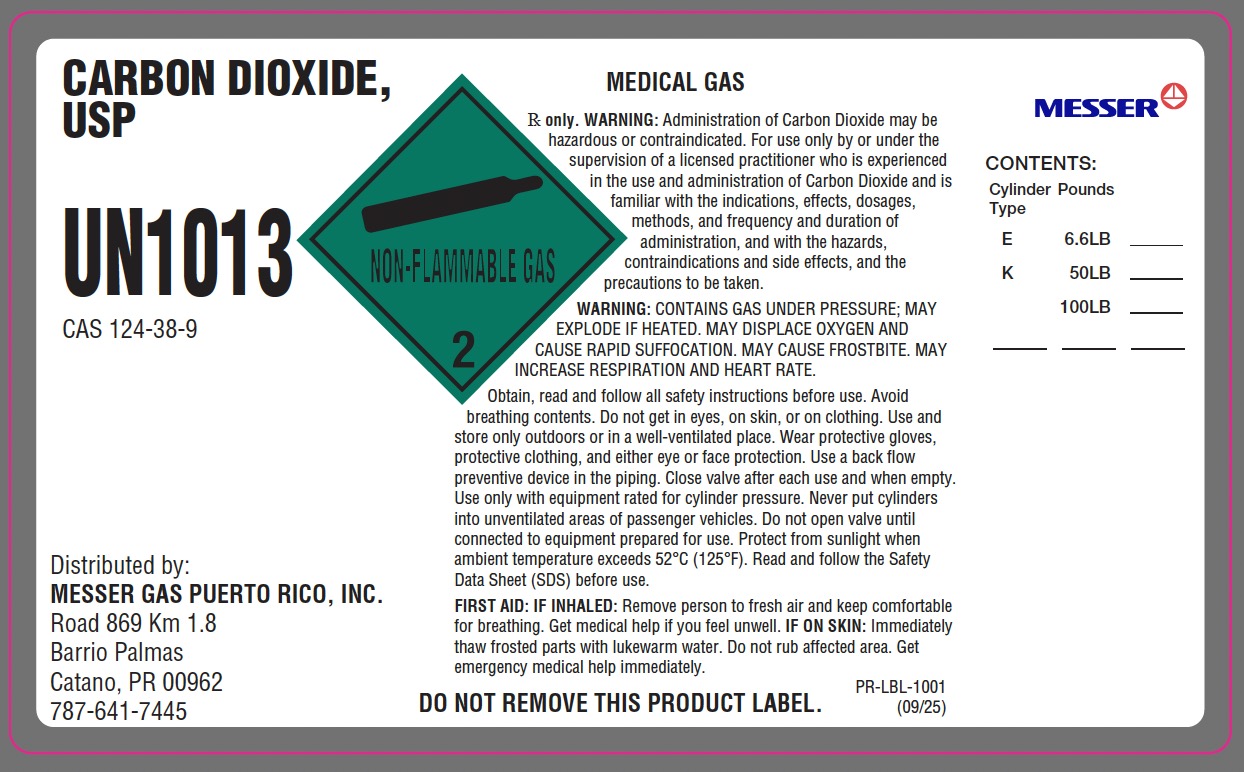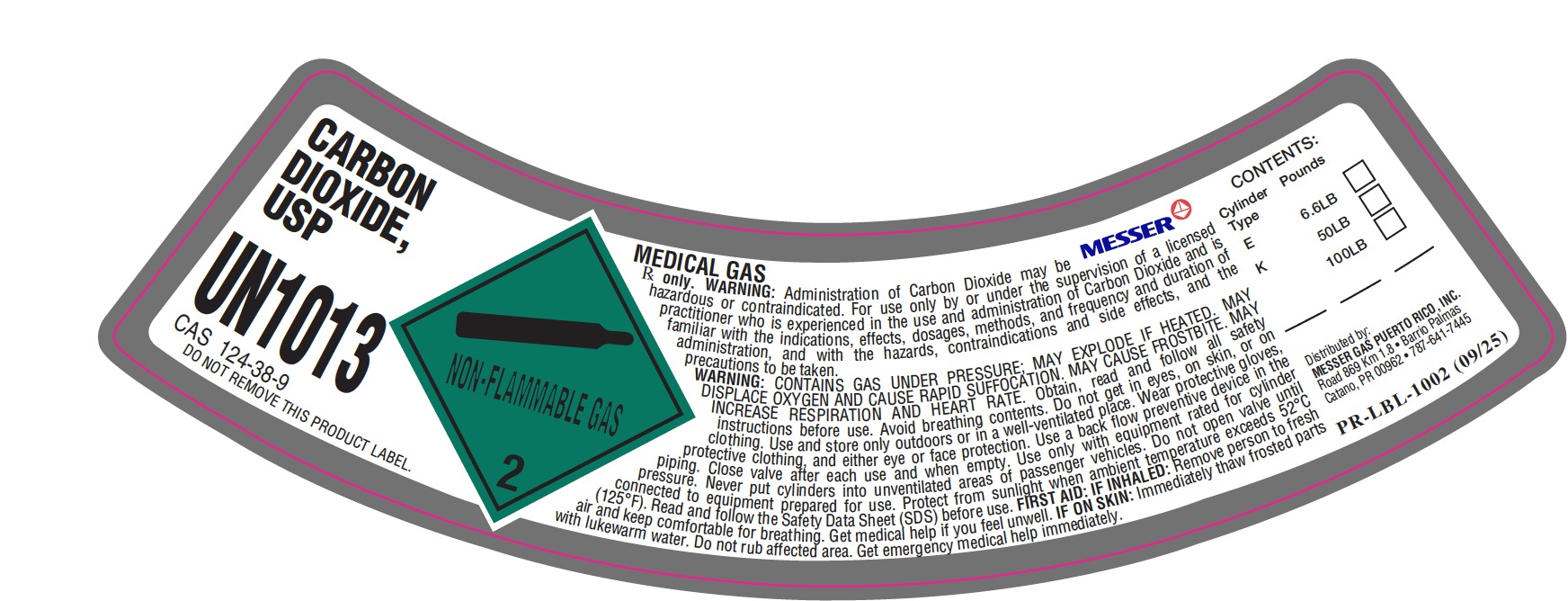 DRUG LABEL: Carbon Dioxide Compressed
NDC: 52374-003 | Form: GAS
Manufacturer: MESSER GAS PUERTO RICO, INC
Category: prescription | Type: HUMAN PRESCRIPTION DRUG LABEL
Date: 20260210

ACTIVE INGREDIENTS: CARBON DIOXIDE 990 mL/1 L

Messer PR - CARBON DIOXIDE, COMPRESSED -003

PACKAGE LABEL

CARBON DIOXIDE, USP

UN1013
CAS 124-38-9

MEDICAL GAS

℞ only. WARNING: Administration of Carbon Dioxide may be hazardous or contraindicated. For use only by or under the supervision of a licensed practitioner who is experienced in the use and administration of Carbon Dioxide and is familiar with the indications, effects, dosages, methods, and frequency and duration of administration, and with the hazards, contraindications and side effects, and the precautions to be taken.

WARNING: CONTAINS GAS UNDER PRESSURE; MAY EXPLODE IF HEATED. MAY DISPLACE OXYGEN AND CAUSE RAPID SUFFOCATION. MAY CAUSE FROSTBITE. MAY INCREASE RESPIRATION AND HEART RATE.

Obtain, read and follow all safety instructions before use. Avoid breathing contents. Do not get in eyes, on skin, or on clothing. Use and store only outdoors or in a well-ventilated place. Wear protective gloves, protective clothing, and either eye or face protection. Use a back flow preventive device in the piping. Close valve after each use and when empty. Use only with equipment rated for cylinder pressure. Never put cylinders into unventilated areas of passenger vehicles. Do not open valve until connected to equipment prepared for use. Protect from sunlight when ambient temperature exceeds 52 C (125 F). Read and follow the Safety Data Sheet (SDS) before use.

FIRST AID: IF INHALED: Remove person to fresh air and keep comfortable for breathing. Get medical help if you feel unwell. IF ON SKIN: Immediately thaw frosted parts with lukewarm water. Do not rub affected area. Get emergency medical help immediately.

Distributed by:
MESSER GAS PUERTO RICO, INC.
Road 869 Km 1.8
Barrio Palmas
Catano, PR 00962
787-641-7445

CONTENTS:
Cylinder Pounds
Type
E 6.6LB
K 50LB
100LB DO NOT REMOVE THIS PRODUCT LABEL.

PACKAGE LABEL

CARBON DIOXIDE, USP

UN1013
CAS 124-38-9
DO NOT REMOVE THIS PRODUCT LABEL.

MEDICAL GAS MESSER
℞ only. WARNING: Administration of Carbon Dioxide may be hazardous or contraindicated. For use only by or under the supervision of a licensed practitioner who is experienced in the use and administration of Carbon Dioxide and is familiar with the indications, effects, dosages, methods, and frequency and duration of the administration, and with the hazards, contraindications and side effects, and the precautions to be taken.

WARNING: CONTAINS GAS UNDER PRESSURE; MAY EXPLODE IF HEATED. MAY DISPLACE OXYGEN AND CAUSE RAPID SUFFOCATION. MAY CAUSE FROSTBITE. MAY INCREASE RESPIRATION AND HEART RATE.

Obtain, read and follow all safety instructions before use. Avoid breathing contents. Do not get in eyes, on skin, or on clothing. Use and store only outdoors or in a well-ventilated place. Wear protective gloves, protective clothing, and either eye or face protection. Use a back flow preventive device in the piping. Close valve after each use and when empty. Use only with equipment rated for cylinder pressure. Never put cylinders into unventilated areas of passenger vehicles. Do not open valve until connected to equipment prepared for use. Protect from sunlight when ambient temperature exceeds 52 C (125 F). Read and follow the Safety Data Sheet (SDS) before use.

FIRST AID: IF INHALED: Remove person to fresh air and keep comfortable for breathing. Get medical help if you feel unwell. IF ON SKIN: Immediately thaw frosted parts with lukewarm water. Do not rub affected area. Get emergency medical help immediately.

CONTENTS:
Cylinder Pounds
Type
E 6.6LB
K 50LB
100LB

Distributed by:
MESSER GAS PUERTO RICO INC.
Road 869 Km 1.8 Barrio Palmas
Catano, PR 00962 787-641-7445